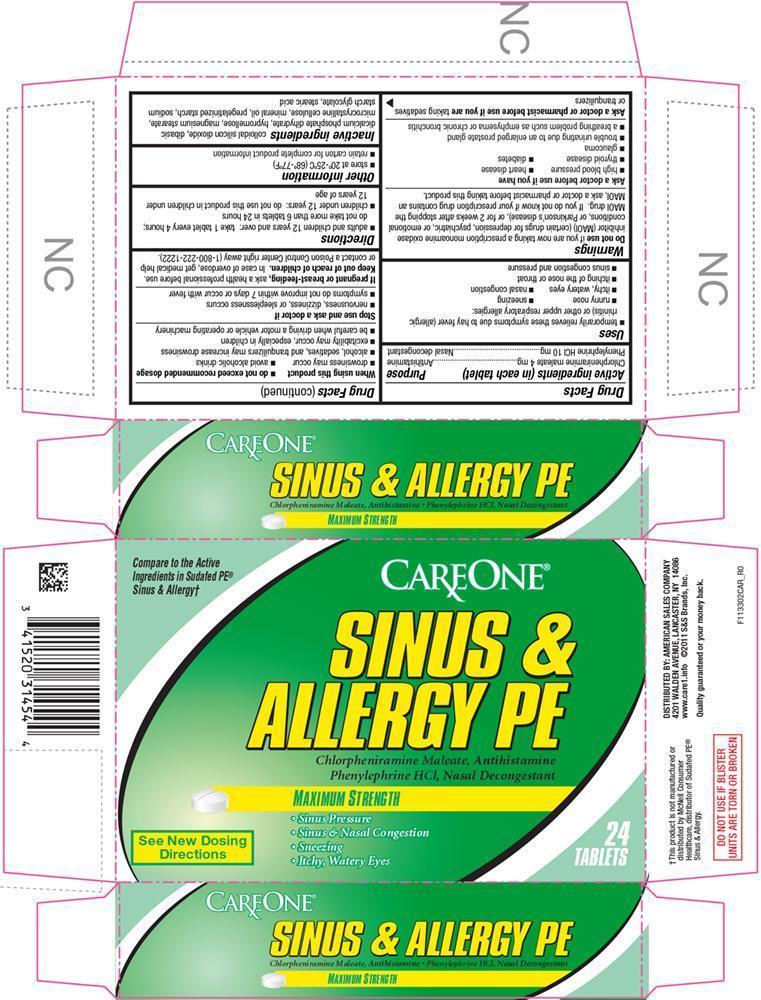 DRUG LABEL: Sinus and Allergy PE
NDC: 41520-602 | Form: TABLET, COATED
Manufacturer: American Sales Company
Category: otc | Type: HUMAN OTC DRUG LABEL
Date: 20150417

ACTIVE INGREDIENTS: CHLORPHENIRAMINE MALEATE 4 mg/1 1; PHENYLEPHRINE HYDROCHLORIDE 10 mg/1 1
INACTIVE INGREDIENTS: SILICON DIOXIDE; CALCIUM PHOSPHATE, DIBASIC, DIHYDRATE; HYPROMELLOSES; MAGNESIUM STEARATE; CELLULOSE, MICROCRYSTALLINE; MINERAL OIL; STARCH, CORN; SODIUM STARCH GLYCOLATE TYPE A CORN; STEARIC ACID

CAR - 1133 - 2015-0401

Drug Facts

ACTIVE INGREDIENT

Active ingredients (in each tablet) | Purpose
Chlorpheniramine maleate 4 mg | Antihistamine
Phenylephrine HCl 10 mg | Nasal decongestant

Uses

- temporarily relieves these symptoms due to hay fever (allergic rhinitis) or other upper respiratory allergies:
  - runny nose
  - sneezing
  - itchy, watery eyes
  - nasal congestion
  - itching of the nose or throat
  - sinus congestion and pressure

Warnings

Do not use if you are now taking a prescription monoamine oxidase inhibitor (MAOI) (certain drugs for depression, psychiatric, or emotional conditions, or Parkinson's disease), or for 2 weeks after stopping the MAOI drug. If you do not know if your prescription drug contains an MAOI, ask a doctor or pharmacist before taking this product.

Ask a doctor before use if you have

- high blood pressure
- heart disease
- thyroid disease
- diabetes
- glaucoma
- trouble urinating due to an enlarged prostate gland
- a breathing problem such as emphysema or chronic bronchitis

Ask a doctor or pharmacist before use if you are taking sedatives or tranquilizers

When using this product

- do not exceed recommended dosage
- drowsiness may occur
- avoid alcoholic drinks
- alcohol, sedatives, and tranquilizers may increase drowsiness
- excitability may occur, especially in children
- be careful when driving a motor vehicle or operating machinery

Stop use and ask a doctor if

- nervousness, dizziness, or sleeplessness occurs
- symptoms do not improve within 7 days or occur with fever

PREGNANCY OR BREAST FEEDING

If pregnant or breast-feeding, ask a health professional before use.

Keep out of reach of children. In case of overdose, get medical help or contact a Poison Control Center right away (1-800-222-1222).

Directions

- adults and children 12 years and over: take 1 tablet every 4 hours; do not take more than 6 tablets in 24 hours
- children under 12 years: do not use this product in children under 12 years of age

Other information

- store at 20°-25°C (68°-77°F)
- retain carton for complete product information

Inactive ingredients

colloidal silicon dioxide, dibasic dicalcium phosphate dihydrate, hypromellose, magnesium stearate, microcrystalline cellulose, mineral oil, pregelatinized starch, sodium starch glycolate, stearic acid

PRINCIPAL DISPLAY PANEL

Compare to the Active Ingredients in Sudafed PE® Sinus & Allergy†

CareOne®

Sinus & Allergy PE

Chlorpheniramine Maleate, Antihistamine

Phenylephrine HCl, Nasal Decongestion

Maximum Strength

Sinus Pressure

Sinus & Nasal Congestion

Sneezing

Itchy, Watery Eyes

See New Dosing Directions

24 Tablets